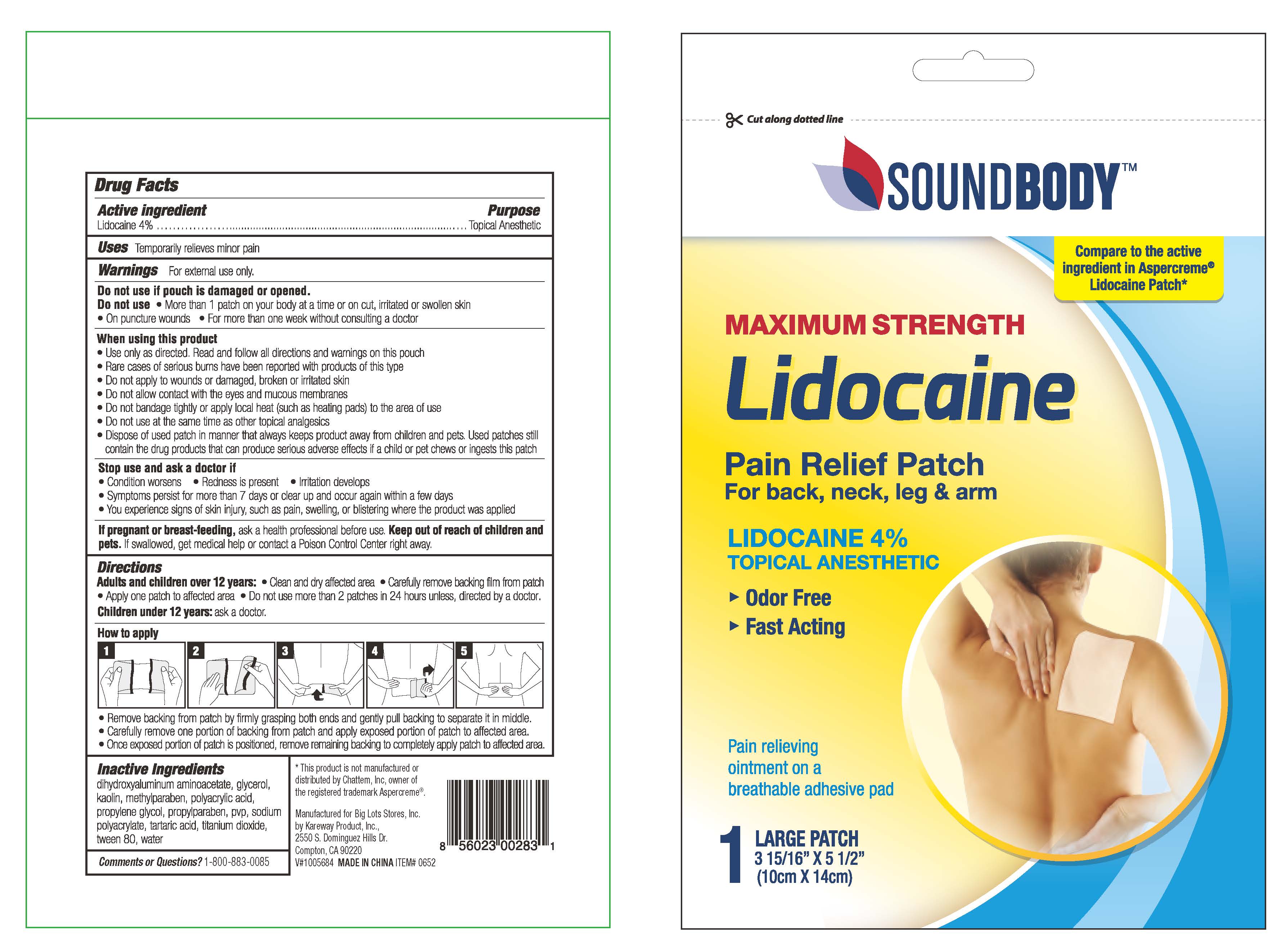 DRUG LABEL: Soundbody
NDC: 67510-0283 | Form: PATCH
Manufacturer: Kareway Product, Inc.
Category: otc | Type: HUMAN OTC DRUG LABEL
Date: 20230217

ACTIVE INGREDIENTS: LIDOCAINE 240 mg/1 1
INACTIVE INGREDIENTS: POLYSORBATE 80; DIHYDROXYALUMINUM AMINOACETATE; GLYCERIN; METHYLPARABEN; KAOLIN; PROPYLPARABEN; PROPYLENE GLYCOL; TARTARIC ACID; TITANIUM DIOXIDE; WATER; POLYACRYLIC ACID (8000 MW); SODIUM POLYACRYLATE (8000 MW); POVIDONE

Sound Body Lidocaine Patch

Active ingredient

Lidocaine 4%

Purposes

Topical Anesthetic

Uses

Temporarily relieves minor pain

Warnings

For external use only

Do Not Use

- more than 1 patch on your body at a time or on cut, irritated or swollen skin
- on puncture wounds
- for more than one week without consulting a doctor

When Using This Product

- use only as directed. Read and follow all directions and warnings on this label.
- rare cases of serious burns have been reported with products of this type
- do not apply to wounds or damaged, broken or irritated skin
- do not allow contact with the eyes and mucous membranes
- do not bandage tightly or apply local heat (such as heating pads) to the area of use
- do not use at the same time as other topical analgesics
- dispose of used patch in manner that always keeps product away from children and pets. Used patches still contain the drug product that can produce serious adverse effects if a child or pet chews or ingests this patch.

Stop Use and Ask a Doctor if

- condition worsens
- redness is present
- irritation develops
- symptoms persist for more than 7 days or clear up and occur again within a few days
- you experience signs of skin injury, such as pain, swelling, or blistering where the product was applied

If Pregnant or Breast-Feeding

ask a health professional before use.

Keep Out of Reach of Children and Pets

If swallowed, get medical help or contact a Poison Control Center right away.

Directions

adults and children over 12 years:

- clean and dry affected area
- remove backing from patch by firmly grasping both ends and gently pulling until backing separates in middle
- carefully remove smaller portion of backing from patch and apply exposed portion of patch to affected area
- once exposed portion of patch is positioned, carefully remove remaining backing to completely apply patch to affected area
- use 2 patch for up to 24 hours

children 12 years or younger: ask a doctor

Inactive Ingredients

dihydroxyaluminum aminoacetate, glycerol, kaolin, methylparaben, polyacrylic acid,

propylene glycol, propylparaben, pvp, sodium polyacrylate, tartaric acid, titanium dioxide, tween 80, water

Package/Label Principal Display Panel

Soundbody

MAXIMUM STRENGTH

LIDOCAINE PATCH

Label